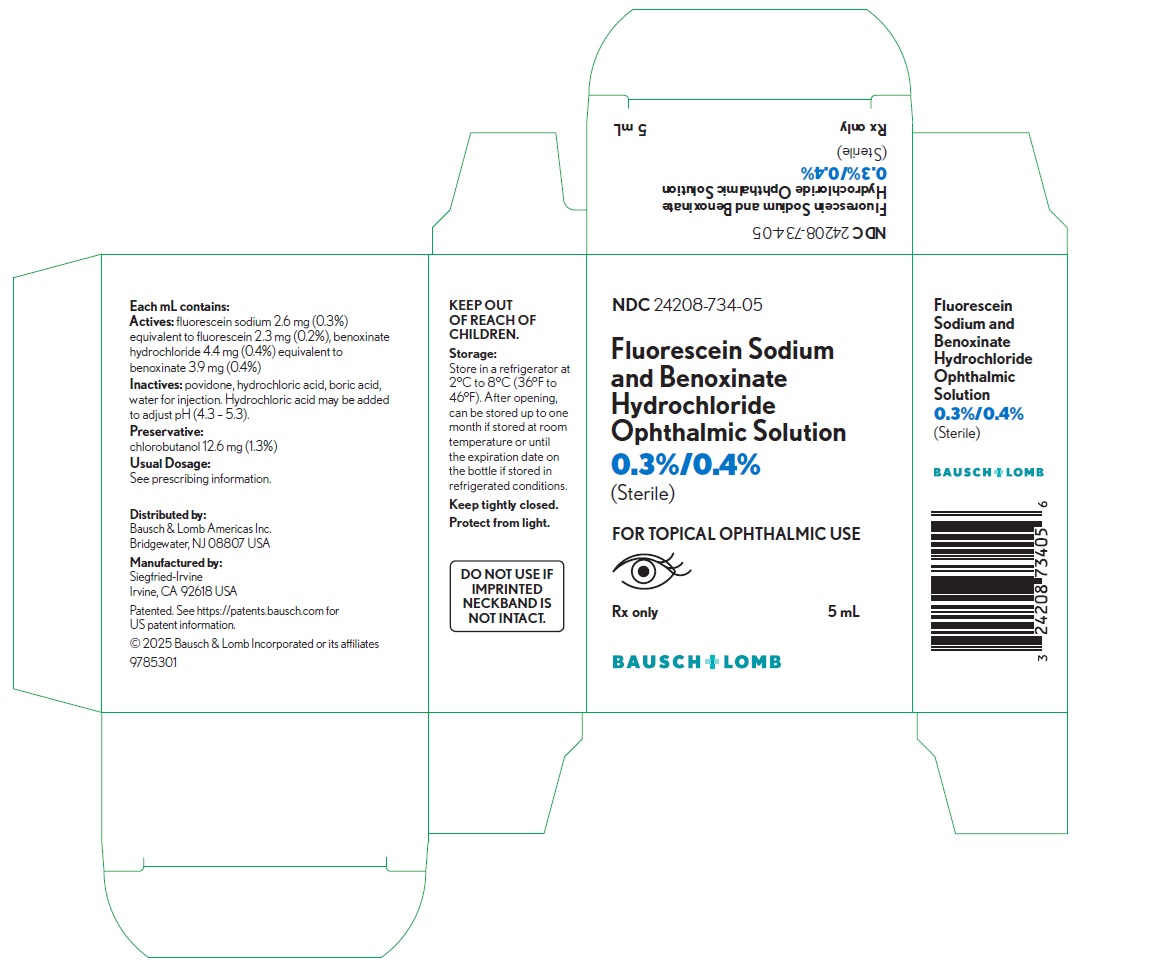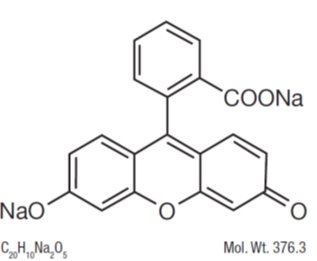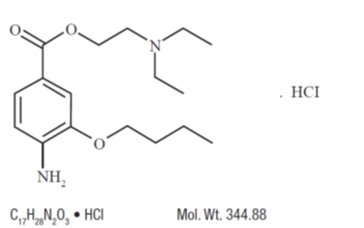 DRUG LABEL: Fluorescein Sodium and Benoxinate Hydrochloride
NDC: 24208-734 | Form: SOLUTION/ DROPS
Manufacturer: Bausch & Lomb Incorporated
Category: prescription | Type: HUMAN PRESCRIPTION DRUG LABEL
Date: 20250512

ACTIVE INGREDIENTS: FLUORESCEIN SODIUM 2.6 mg/1 mL; BENOXINATE HYDROCHLORIDE 4.4 mg/1 mL
INACTIVE INGREDIENTS: POVIDONE, UNSPECIFIED; BORIC ACID; WATER

HIGHLIGHTS OF PRESCRIBING INFORMATION

These highlights do not include all the information needed to use FLUORESCEIN SODIUM AND BENOXINATE HYDROCHLORIDE OPHTHALMIC SOLUTION, 0.3%/0.4% safely and effectively. See full prescribing information for FLUORESCEIN SODIUM AND BENOXINATE HYDROCHLORIDE OPHTHALMIC SOLUTION, 0.3%/0.4%.
FLUORESCEIN SODIUM AND BENOXINATE HYDROCHLORIDE OPHTHALMIC SOLUTION, 0.3%/0.4%, for topical ophthalmic use
Initial U.S. Approval: 2017

1 INDICATIONS AND USAGE

Fluorescein Sodium and Benoxinate Hydrochloride Ophthalmic Solution, 0.3%/0.4% is a combination of fluorescein sodium, a disclosing agent and benoxinate hydrochloride, a local ester anesthetic indicated for procedures in adult and pediatric patients requiring a disclosing agent in combination with a topical ophthalmic anesthetic. (1)

2 DOSAGE AND ADMINISTRATION

Instill 1 to 2 drops topically in the eye as needed to achieve adequate anesthesia. (2)

3 DOSAGE FORMS AND STRENGTHS

Ophthalmic solution containing fluorescein sodium 2.6 mg/mL (0.3%) and benoxinate hydrochloride 4.4 mg/mL (0.4%). (3)

4 CONTRAINDICATIONS

Known hypersensitivity to any component of this product. (4)

5 WARNINGS AND PRECAUTIONS

- Corneal Toxicity: Prolonged use or abuse may lead to corneal epithelial toxicity and manifest as epithelial defects which may progress to permanent corneal damage. (Error! Hyperlink reference not valid.)
- Corneal Injury: Patients should not touch the eye for approximately 20 minutes after using anesthetic as accidental injuries can occur due to insensitivity of the eye. (5.2)

6 ADVERSE REACTIONS

The most common ocular adverse events are: stinging, burning and conjunctival redness. (6)

To report SUSPECTED ADVERSE REACTIONS, contact Bausch & Lomb Incorporated at 1-800-553-5340 or FDA at 1-800-FDA-1088 or www.fda.gov/medwatch.

FULL PRESCRIBING INFORMATION

1 INDICATIONS AND USAGE

Fluorescein Sodium and Benoxinate Hydrochloride Ophthalmic Solution, 0.3%/0.4% is indicated for ophthalmic procedures in adult and pediatric patients requiring a disclosing agent in combination with a topical ophthalmic anesthetic agent.

2 DOSAGE AND ADMINISTRATION

Instill 1 to 2 drops topically in the eye as needed.

3 DOSAGE FORMS AND STRENGTHS

Fluorescein Sodium and Benoxinate Hydrochloride Ophthalmic Solution, 0.3%/0.4% is a yellow to orange-red ophthalmic solution containing fluorescein sodium 2.6 mg/mL (0.3%) and benoxinate hydrochloride 4.4 mg/mL (0.4%).

4 CONTRAINDICATIONS

Fluorescein Sodium and Benoxinate Hydrochloride Ophthalmic Solution, 0.3%/0.4% is contraindicated in patients with known hypersensitivity to any component of this product.

5 WARNINGS AND PRECAUTIONS

5.1 Corneal Toxicity

Prolonged use or abuse may lead to corneal epithelial toxicity and may manifest as epithelial defects which may progress to permanent corneal damage with accompanying visual loss.

5.2 Corneal Injury Due to Insensitivity

Patients should not touch the eye for approximately 20 minutes after using this anesthetic as accidental injuries can occur due to insensitivity of the eye.

6 ADVERSE REACTIONS

The following serious ocular adverse reactions are described elsewhere in the labeling:

- Corneal Toxicity [see Warnings and Precautions (5.1)]
- Corneal Injury Due to Insensitivity [see Warnings and Precautions (5.2)]

The following adverse reactions have been identified following use of Fluorescein Sodium and Benoxinate Hydrochloride Ophthalmic Solution, 0.3%/0.4%: ocular hyperemia, burning, stinging, eye irritation, blurred vision and punctate keratitis. Because these reactions are reported voluntarily from a population of uncertain size, it is not always possible to reliably estimate their frequency or establish a causal relationship to drug exposure.

8 USE IN SPECIFIC POPULATIONS

8.1 Pregnancy

Risk Summary

There are no available data on the use of Fluorescein Sodium and Benoxinate Hydrochloride Ophthalmic Solution, 0.3%/0.4% in pregnant women to inform any drug associated risk.

Adequate animal reproduction studies have not been conducted with fluorescein sodium and/or benoxinate hydrochloride. Fluorescein Sodium and Benoxinate Hydrochloride Ophthalmic Solution, 0.3%/0.4% should be given to a pregnant woman only if clearly needed.

8.2 Lactation

Risk Summary

There are no data on the presence of fluorescein sodium or benoxinate hydrochloride in human milk after ocular administration of Fluorescein Sodium and Benoxinate Hydrochloride Ophthalmic Solution, 0.3%/0.4%, the effects on the breastfed infant, or the effects on milk production.

The developmental and health benefits of breastfeeding should be considered, along with the mother’s clinical need for Fluorescein Sodium and Benoxinate Hydrochloride Ophthalmic Solution, 0.3%/0.4%, and any potential adverse effects on the breastfed infant from Fluorescein Sodium and Benoxinate Hydrochloride Ophthalmic Solution, 0.3%/0.4%.

8.4 Pediatric Use

The safety and effectiveness of Fluorescein Sodium and Benoxinate Hydrochloride Ophthalmic Solution, 0.3%/0.4% have been established for pediatric patients. Use of Fluorescein Sodium and Benoxinate Hydrochloride Ophthalmic Solution, 0.3%/0.4% is supported in pediatric patients by evidence from adequate and well controlled studies.

8.5 Geriatric Use

No overall differences in safety or effectiveness have been observed between elderly and younger patients.

11 DESCRIPTION

Fluorescein Sodium and Benoxinate Hydrochloride Ophthalmic Solution, 0.3%/0.4% is a sterile solution containing a disclosing agent in combination with a short-acting ester anesthetic for topical ophthalmic use.

Fluorescein sodium is represented by the following structural formula:

Chemical Name: 3’,6’ Dihydroxy-3H-spiro[isobenzofuran-1,9-xanthen]-3-one disodium salt.

Benoxinate hydrochloride is represented by the following structural formula:

Chemical Name: 2-(Diethylamino) ethyl 4-amino-3-butoxybenzoate hydrochloride.

Each mL of Fluorescein Sodium and Benoxinate Hydrochloride Ophthalmic Solution 0.3%/0.4% contains:

- Active ingredients:fluorescein sodium 2.6 mg (0.3%) equivalent to fluorescein 2.3 mg (0.2%), benoxinate hydrochloride 4.4 mg (0.4%) equivalent to benoxinate 3.9 mg (0.4%)
- Preservative:chlorobutanol 12.6 mg (1.3%)
- Inactive ingredients:povidone, hydrochloric acid, boric acid, water for injection. Hydrochloric acid may be added to adjust pH (4.3 – 5.3).

12 CLINICAL PHARMACOLOGY

12.2 Pharmacodynamics

Maximal corneal anesthesia usually occurs in about 5-45 seconds and lasts about 20 minutes after single administration. The anesthetic effect may be extended by subsequent administration 10-20 minutes after the last administration.

13 NONCLINICAL TOXICOLOGY

13.1 Carcinogenesis, Mutagenesis, Impairment of Fertility

Studies to evaluate the mutagenic or carcinogenic potential of Fluorescein Sodium and Benoxinate Hydrochloride Ophthalmic Solution, 0.3%/0.4% have not been conducted. Studies to evaluate impairment of fertility have not been conducted.

14 CLINICAL STUDIES

Controlled clinical studies in adults and pediatric patients have demonstrated that topical administration of Fluorescein Sodium and Benoxinate Hydrochloride Ophthalmic Solution, 0.3%/0.4% enables visualization and corneal anesthesia sufficient to enable applanation tonometry, tear fluid dynamics evaluation and short conjunctival and corneal procedures. Maximal corneal anesthesia usually occurs in about 5-45 seconds and lasts about 20 minutes after single administration.

16 HOW SUPPLIED/STORAGE AND HANDLING

Fluorescein Sodium and Benoxinate Hydrochloride Ophthalmic Solution, 0.3%/0.4% is supplied as a sterile, aqueous, topical ophthalmic solution with a fill volume of 5 mL in a 6 mL amber glass bottle and a black polypropylene cap with a sterilized rubber dropper bulb and glass pipette.

NDC 24208-734-05

Storage:Store in a refrigerator at 2°C to 8°C (36°F to 46°F). Protect from light. After opening, can be stored up to one month if stored at room temperature or until the expiration date on the bottle if stored in refrigerated conditions. Keep tightly closed.

17 PATIENT COUNSELING INFORMATION

Accidental Injury Precaution

Advise patients not to touch their eyes for approximately 20 minutes after application. Their eyes will be insensitive due to the effect of the anesthetic, and care should be taken to avoid accidental injuries.

Distributed by:
Bausch & Lomb Americas Inc.
Bridgewater, NJ 08807 USA

Manufactured by:
Siegfried-Irvine
Irvine, CA 92618 USA

Patented. See https://patents.bausch.comfor US patent information.

© 2022 Bausch & Lomb Incorporated or its affiliates

9785500

PACKAGE/LABEL PRINCIPAL DISPLAY PANEL

NDC24208-734-05

Fluorescein Sodium

and Benoxinate

Hydrochloride

Ophthalmic Solution

0.3%/0.4%

(Sterile)

FOR TOPICAL OPHTHALMIC USE

[Eye Image]

Rx only 5 mL

BAUSCH + LOMB

9785301